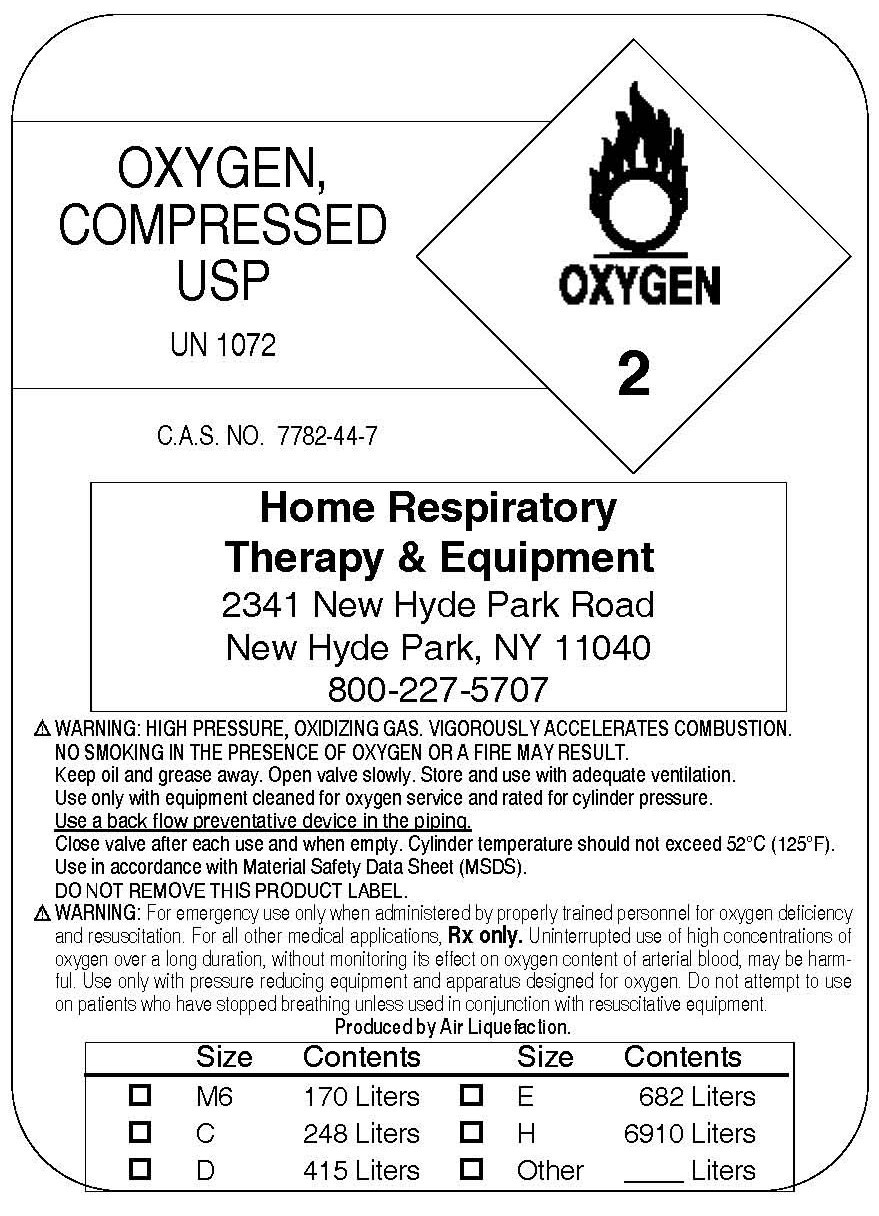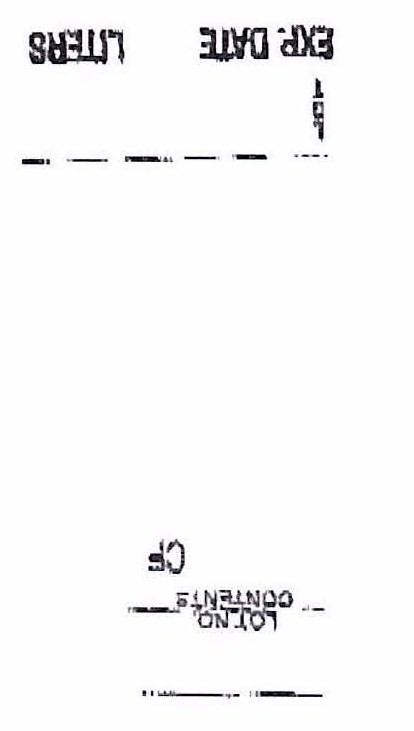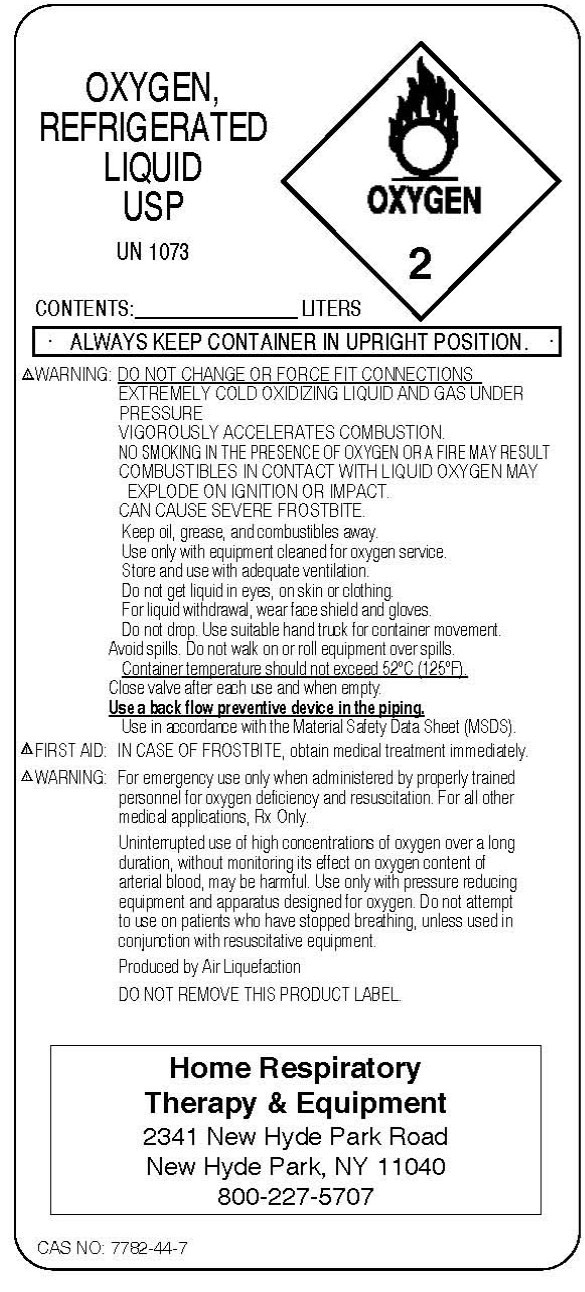 DRUG LABEL: Oxygen
NDC: 63043-0001 | Form: GAS
Manufacturer: Home Respiratory Therapy and Equipment, Inc.
Category: prescription | Type: HUMAN PRESCRIPTION DRUG LABEL
Date: 20091118

ACTIVE INGREDIENTS: Oxygen 99 L/100 L

Oxygen